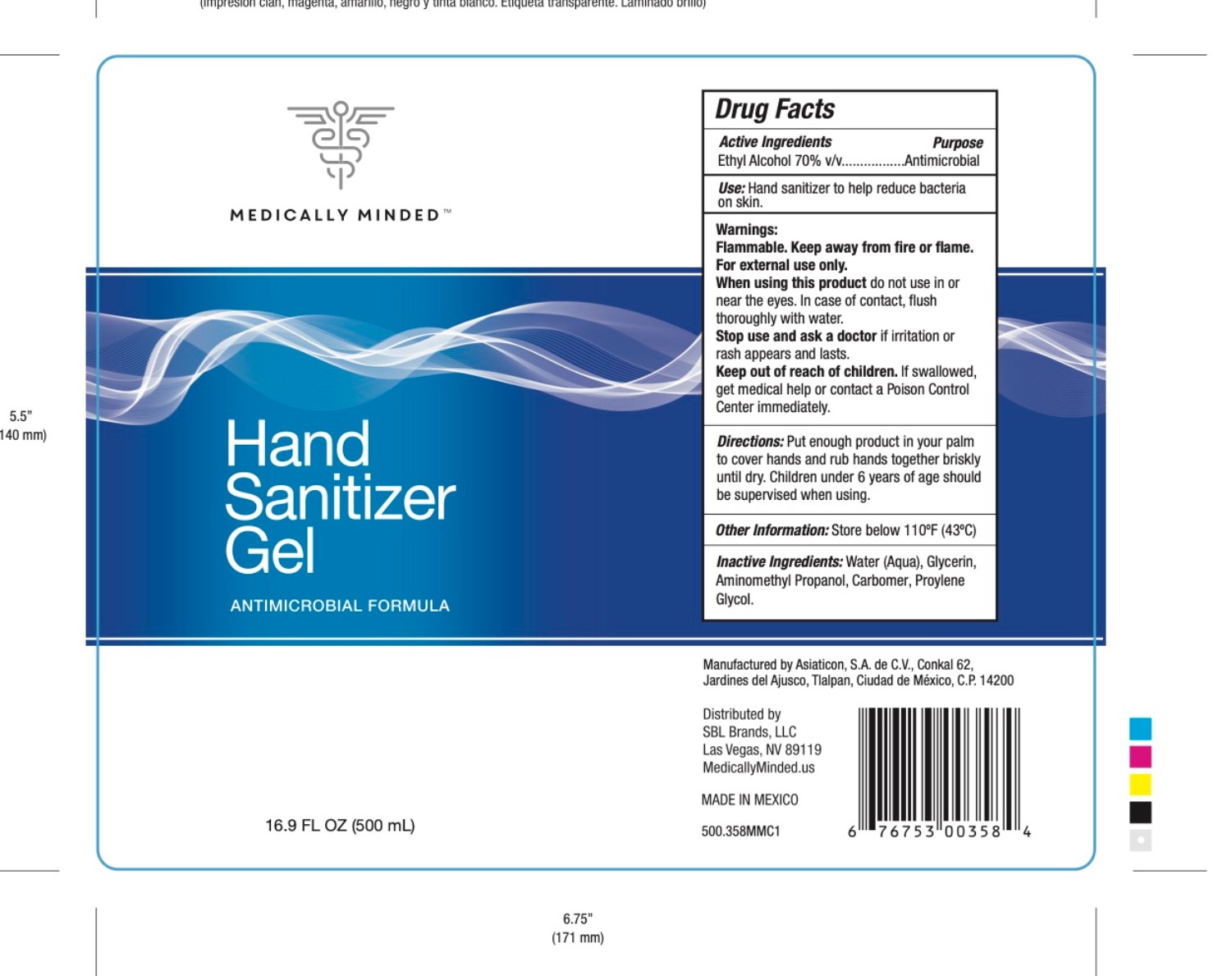 DRUG LABEL: Hand sanitizer
NDC: 75192-600 | Form: GEL
Manufacturer: Asiaticon, S.A. de C.V.
Category: otc | Type: HUMAN OTC DRUG LABEL
Date: 20200430

ACTIVE INGREDIENTS: ALCOHOL 70 mL/100 mL
INACTIVE INGREDIENTS: AMINOMETHYLPROPANOL 0.5 mL/100 mL; GLYCERIN 0.85 mL/100 mL; PROPYLENE GLYCOL 0.3 mL/100 mL; POLYACRYLIC ACID (8000 MW) 0.4 mL/100 mL; WATER 27.95 mL/100 mL

Directions

Put enough product in your palm to cover hands and rub hands together briskly until dry.

Children under 6 years of age should be supervised when using.

Warnings

Flammable. Keep away from fire or flame.

For external use only

Inactive ingredients

Water, glycerin, aminomethyl propanol, carbomer, propylene glycol

Use

Hand sanitizer to help reduce bacteria on skin

KEEP OUT OF REACH OF CHILDREN

If swallowed, get medical help or contact a Poison Control Center immediately

Purpose

Hand sanitizer. Antimicrobial

Active Ingredient(s)

Ethyl alcohol 70% v/v

PACKAGE LABEL

500 mL NDC: 75192-600-01